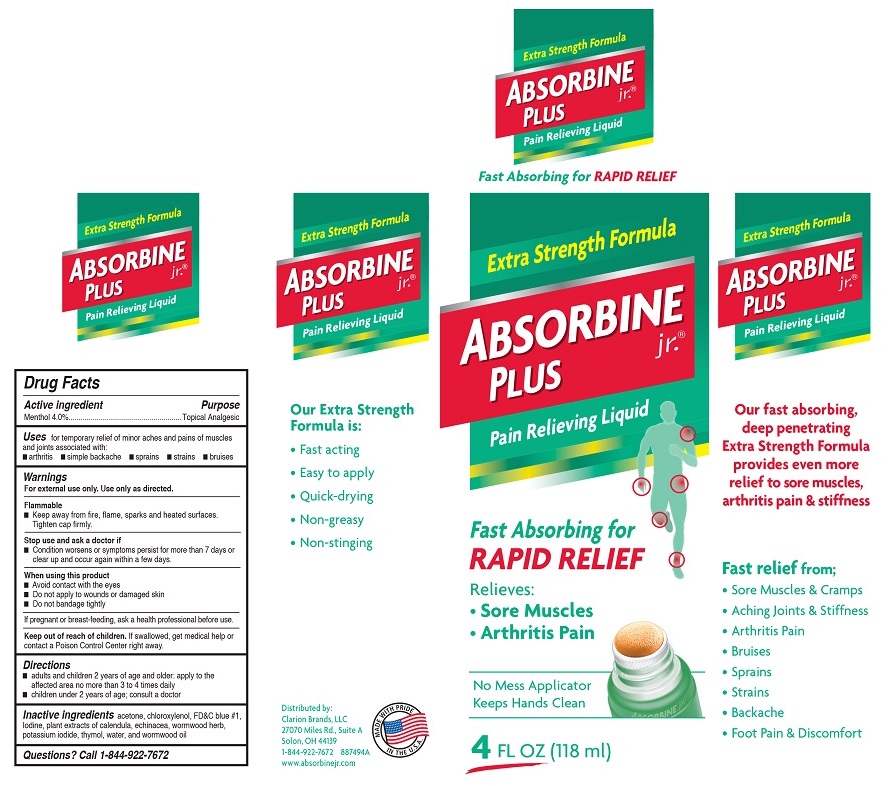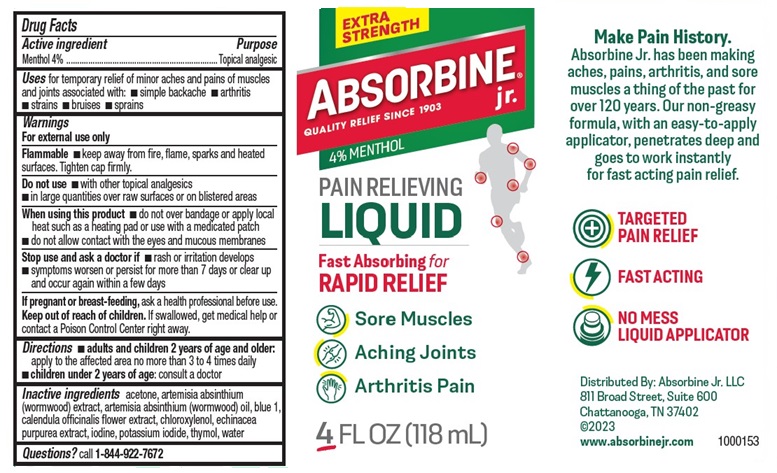 DRUG LABEL: Absorbine Jr.
NDC: 69693-411 | Form: LIQUID
Manufacturer: Clarion Brands, LLC
Category: otc | Type: HUMAN OTC DRUG LABEL
Date: 20251223

ACTIVE INGREDIENTS: MENTHOL 4 g/100 mL
INACTIVE INGREDIENTS: ACETONE; FD&C BLUE NO. 1; IODINE; CALENDULA OFFICINALIS FLOWER; ECHINACEA, UNSPECIFIED; WORMWOOD; POTASSIUM IODIDE; THYMOL; WATER; WORMWOOD OIL

Absorbine jr.®Plus
Drug Facts

Active Ingredient

Menthol 4.0%

Purpose

Topical Analgesic

Uses

For temporary relief of minor aches and pains of muscles and joints associated with:

- arthritis
- simple backache
- sprains
- strains
- bruises

Warnings

For external use only. Use only as directed.

Flammable

- Keep away from fire, flame, sparks and heated surfaces. Tighten cap firmly.

Stop use and ask a doctor if

- Condition worsens or symptoms persist for more than 7 days or clear up and occur again within a few days.

When using this product

- Avoid contact with the eyes
- Do not apply to wounds or damaged skin
- Do not bandage tightly

If pregnant or breast feeding,

ask a health professional before use.

Keep out of reach of children.

If swallowed, get medical help or contact a Poison Control Center right away.

Directions

- adults and children 2 years of age and older: apply to the affected area no more than 3 to 4 times daily
- children under 2 years of age; consult a doctor

Inactive Ingredients

acetone, chloroxylene, FD&C blue #1, Iodine, plant extracts of calendula, echinacea, wormwood herb, potassium iodide, thymol, water, and wormwood oil

Questions?

Call 1-844-922-7672

Principal Display Panel

Extra Strength Formula
ABSORBINE jr.®PLUS
Pain Relieving Liquid
Fast Absorbing for Rapid Relief
Relieves:
• Sore Muscles
• Arthritis Pain
No Mess Applicator Keeps Hands Clean
4 FL OZ (118 ml)
Our fast absorbing, deep penetrating Extra Strength Formula provides even more relief to sore muscles, arthritis pain & stiffness
Fast relief from;
•Sore Muscles & Cramps
•Aching Joints & Stiffness
•Arthritis Pain
•Bruises
•Sprains
•Strains
•Backache
•Foot Pain & Discomfort
Our Extra Strength Formula is:
• Fast acting
•Easy to apply
•Quick-drying
•Non-greasy
• Non-stinging
MADE WITH PRIDE IN THE U.S.A.
Distributed by:
Clarion Brands, LLC
27070 Miles Rd., Suite A
Solon, OH 44139
1-844-922-7672 88749A
www.absorbinejr.com

Extra Strength
ABSORBINE® jr.
QUALITY RELIEF SINCE 1903
4% MENTHOL
Pain Relieving
Liquid
Fast Absorbing for
Rapid Relief
• Sore Muscles
• Aching Joints
• Arthritis Pain
4 FL OZ (118 ml)
Make Pain History.
Absorbine Jr. has been making
aches, pains, arthritis, and sore
muscles a thing of the past for
over 120 years. Our non-greasy
formula, with an easy-to-apply
applicator, penetrates deep and
goes to work instantly
for fast acting pain relief.
• TARGETED PAIN RELIEF
• FAST ACTING
• NO MESS LIQUID APPLICATOR
Distributed by: Absorbine Jr. LLC
811 Broad Street, Suite 600
Chattanooga, TN 37402
@2023
www.absorbinejr.com
1000153